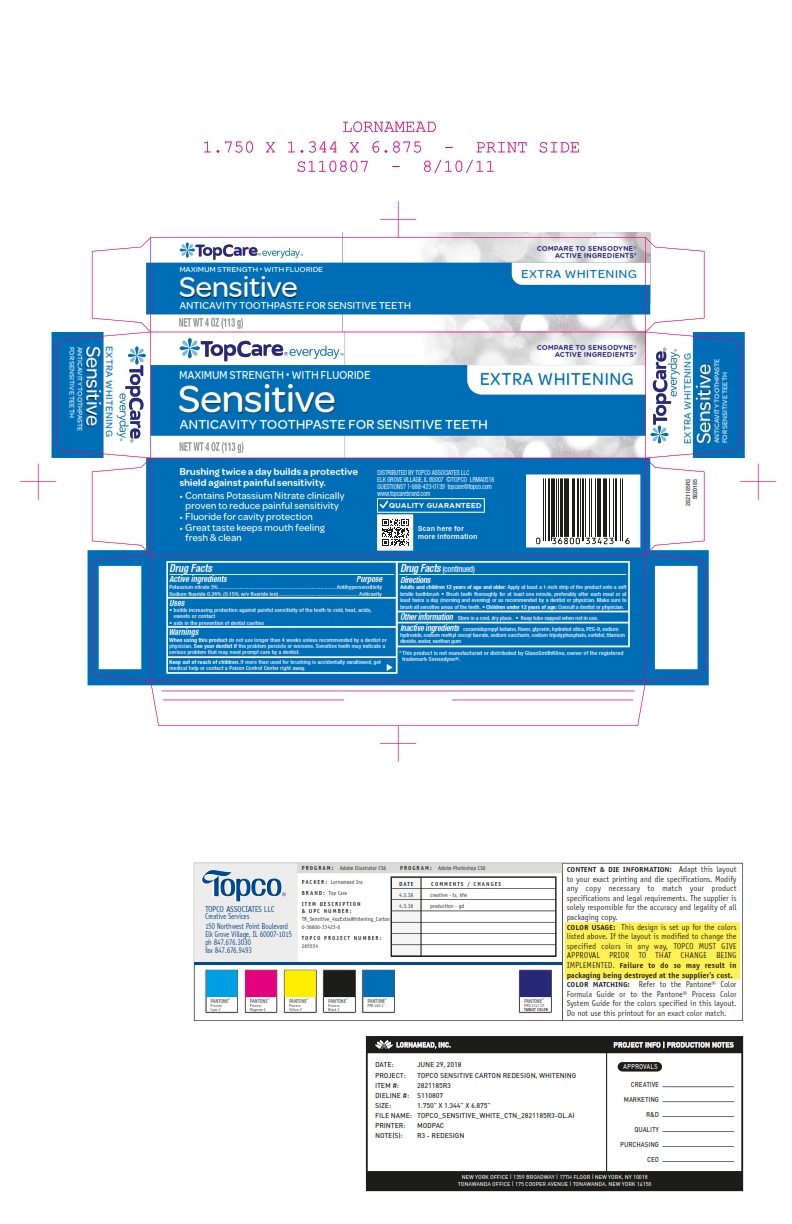 DRUG LABEL: TopCare Sensitive
NDC: 36800-451 | Form: PASTE, DENTIFRICE
Manufacturer: TOPCO Assoc. LLC
Category: otc | Type: HUMAN OTC DRUG LABEL
Date: 20250808

ACTIVE INGREDIENTS: SODIUM FLUORIDE 0.15 g/100 g; POTASSIUM NITRATE 5 g/100 g
INACTIVE INGREDIENTS: WATER; SACCHARIN SODIUM; SODIUM TRIPOLYPHOSPHATE; POLYETHYLENE GLYCOL, UNSPECIFIED; SORBITOL; TITANIUM DIOXIDE; SODIUM HYDROXIDE; GLYCERIN; XANTHAN GUM; HYDRATED SILICA; COCAMIDOPROPYL BETAINE; SODIUM METHYL COCOYL TAURATE

5820185 TopCare Max Str Sensitive Extra Whitening

Drug Facts

Active ingredients

Potassium nitrate 5%

Sodium fluoride 0.24% (0.15% w/v fluoride ion)

Purpose

Antihypersensitivity

Anticavity

Uses

- builds increasing protection against painful sensitivity of the teeth to cold, heat, acids, sweets or contact
- aids in the prevention of dental cavities

Warnings

When using this product do not use longer than 4 weeks unless recommended by a dentist or physician.

STOP USE

See your dentist if the problem worsens. Sensitive teeth may indicate a serious problem that may need prompt care by a dentist.

Keep out of reach of children. If more than used for brushing is accidentally swallowed, get medical help or contact a Poison Control Center right away.

Directions

Adults and children 12 years of age and older: Apply at least 1-inch strip of the product onto a soft bristle toothbrush.

- Brush teeth thoroughly for at least one minute, preferably after each meal or at least twice a day (morning and evening) or as recommended by a dentist or physican. Make sure to brush all sensitive areas of the teeth.
- Children under 12 years of age: Consult a dentist or physician.

Other information

Store in a cool dry place. Keep tube capped when not in use.

INACTIVE INGREDIENT

Inactive ingredients cocamidopropyl betaine, flavor, glycerin, hydrated silica, PEG-8, sodium hydroxide, sodium methyl cocoyl taurate, sodium saccharin, sodium tripolyphosphate, sorbitol, titanium dioxide, water, xanthan gum

DISTRIBUTED BY TOPCO ASSOCIATES LLC

ELK GROVE VILLAGE, IL 60007

QUESTIONS? 1-888-423-0139 topcare@topco.com

www.topcarebrand.com